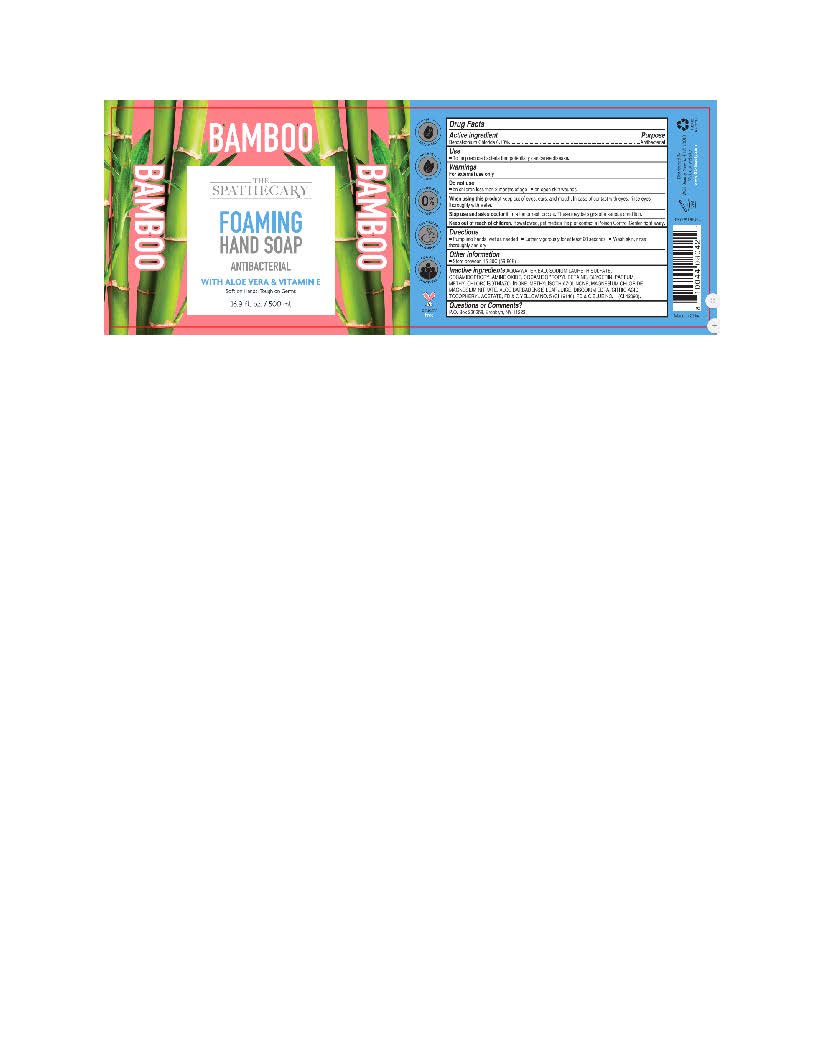 DRUG LABEL: The Spathecary Foaming Bamboo
NDC: 73166-113 | Form: SOAP
Manufacturer: Larry (Xiamen) Hi Tech Co., Ltd
Category: otc | Type: HUMAN OTC DRUG LABEL
Date: 20201013

ACTIVE INGREDIENTS: BENZALKONIUM CHLORIDE 0.65 g/500 mL
INACTIVE INGREDIENTS: ALOE VERA LEAF; MAGNESIUM NITRATE; MAGNESIUM CHLORIDE ANHYDROUS; ANHYDROUS CITRIC ACID; GLYCERIN; WATER; .ALPHA.-TOCOPHEROL ACETATE; COCAMIDOPROPYL BETAINE; METHYLCHLOROISOTHIAZOLINONE; METHYLISOTHIAZOLINONE; SODIUM LAURETH SULFATE; DISODIUM EDTA-COPPER; FD&C YELLOW NO. 5; FD&C BLUE NO. 1; COCAMIDOPROPYLAMINE OXIDE

The Spathecary Foaming Hand Soap Bamboo

Active Ingredient

Benzalkonium Chloride 0.13%

Purpose

Antibacterial

Uses

to help reduce bacteria that potentially can cause disease.

Warnings

For external use only.

When using this product. Avoid contact with eyes. In case of eye contact, rinse eyes thoroughly with water.

Stop use and ask a doctor

if irritation or rash occurs. These may be signs of a serious condition.

Keep out of reach of children.

If swallowed, get medical help or contact a Poison Control Center right away

Directions

Pump into hands, wet as needed. Lather vigorously for at least 20 seconds. Wash skin, rinse thoroughly, and dry.

Other Information

Store between 15-30C (59-86F)

Inactive Ingredients

aqua/water/EAU, Sodium Laureth Sulfate, cocamidopropylamine oxide, cocamidopropyl betaine, glycerin, parfum, methylchloroisothiazolinone, Methylisothiazolinone, Magnesium chloride, Magnesium nitrate, Aloe Barbadensis Leaf Juice, Disodium EDTA, Citric Acid, Tocopheryl Acetate, FD &C yellow No.5 (CI 19140), FD&C Blue No. 1 (CI 42090)

Questions or Comments?

P.O. Box 230258, Brooklyn, NY 11223